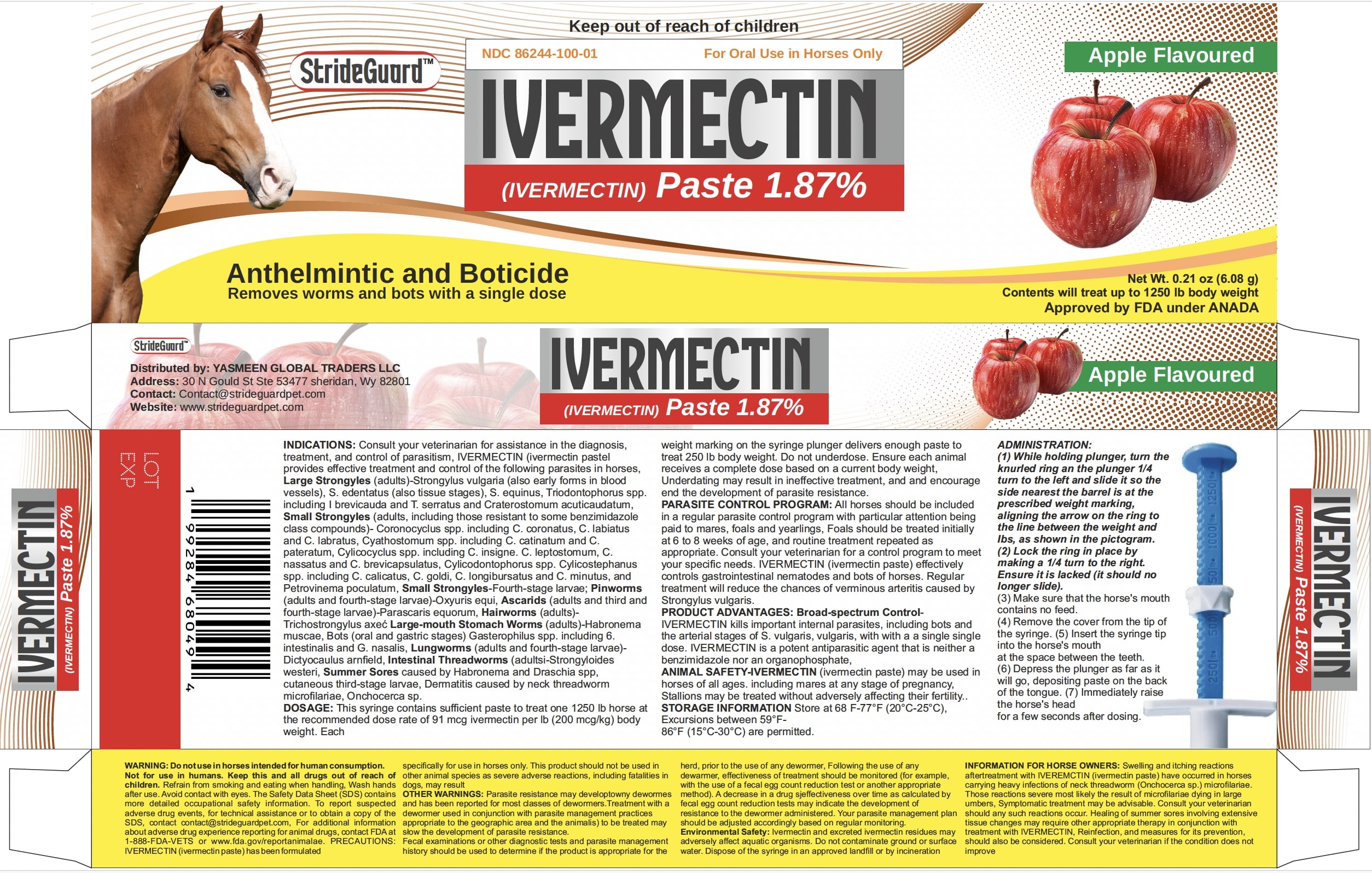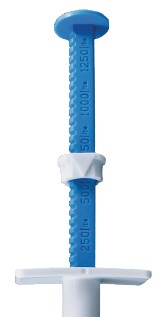 DRUG LABEL: Ivermectin
NDC: 86244-100 | Form: PASTE
Manufacturer: YASMEEN GLOBAL TRADERS LLC
Category: animal | Type: OTC ANIMAL DRUG LABEL
Date: 20260211

ACTIVE INGREDIENTS: IVERMECTIN 18.7 mg/1 g

StrideGuardTM (IVERMECTIN) Paste 1.87%

DESCRIPTION

For Oral Use in Horses Only

StrideGuardTM (IVERMECTIN) Paste 1.87%

Net Wt. 0.21 oz (6.08)
Contents will treat up to 1250 lb body weight

Approved by FDA under # 200-336

Apple Flavored

INDICATIONS AND USAGE

INDICATIONS: Consult your veterinarian for assistance in the diagnosis, treatment, and control of parasitism. IVERMECTIN (ivermectin paste) provides effective treatment and control of the following parasites in horses. Large Strongyles (adults)- Strongylus vulgaris (also early forms in blood vessels), S. edentatus (also tissue stages), S. equinus, Triodontophorus spp. including T. brevicauda and T. serratus and Craterostomum acuticaudatum; Small Strongyles (adults, including those resistant to some benzimidazole class compounds)-Coronocyclus spp. including C. coronatus, C. labiatus and C. labratus, Cyathostomum spp. including C. catinatum and C. pateratum, Cylicocyclus spp. including C. insigne, C. leptostomum, C. nassatus, and C. brevicapsulatus, Cylicodontophorus spp., Cylicostephanus spp. including C. calicatus, C. goldi, C. longibursatus and C. minutus, and Petrovinema poculatum; Small Strongyles - Fourth-stage larvae; Pinworms (adults and fourth-stage larvae)-Oxyuris equi; Ascarids (adults and third- and fourth-stage larvae)- Parascaris equorum; Hairworms (adults)-Trichostrogylus axei; Large-mouth Stomach Worms (adults)- Habronema muscae; Bots (oral and gastric stages)-Gasterophilus spp. including G. intestinalis and G. nasalis; Lungworms (adults and fourth-stage larvae)- Dictyocaulus arnfieldi; Intestinal Threadworms (adults)- Strongyloides westeri; Summer Sores caused by Habronema and Draschia spp. cutaneous third-stage larvae; Dermatitis caused by neck threadworm microfilariae, Onchocerca sp.

DOSAGE AND ADMINISTRATION

DOSAGE: This syringe contains sufficient paste to treat one 1250 lb horse at the recommended dose rate of 91 mcg ivermectin per lb (200 mcg/kg) body weight. Each weight marking on the syringe plunger delivers enough paste to treat 250 lb body weight.

Do not underdose. Ensure each animal receives a complete dose based on a current body weight. Underdosing may result in ineffective treatment, and encourage the development of parasite resistance.

CONTROL PROGRAM: All horses should be included in a regular parasite control program with particular attention being paid to mares, foals and yearlings. Foals should be treated initially at 6 to 8 weeks of age, and routine treatment repeated as appropriate. Consult your veterinarian for a control program to meet your specific needs. IVERMECTIN (ivermectin paste) effectively controls gastrointestinal nematodes and bots of horses. Regular treatment will reduce the chances of verminous arteritis caused by Strongylus vulgaris.

PRODUCT ADVANTAGES: Broad-spectrum Control - IVERMECTIN kills important internal parasites, including bots and the arterial stages of S. vulgaris, with a single dose. IVERMECTIN is a potent antiparasitic agent that is neither a benzimidazole nor an organophosphate.

WARNINGS

ANIMAL SAFETY: IVERMECTIN (ivermectin paste) may be used in horses of all ages, including mares at any stage of pregnancy. Stallions may be treated without adversely affecting their fertility.

STORAGE AND HANDLING

STORAGE INFORMATION: Store at 68°F - 77°F (20°C - 25°C). Excursions between 59°F - 86°F (15°C - 30°C) are permitted.

ADMINISTRATION:

(1) While holding plunger, turn the knurled ring on the plunger 1/4 turn to the left and slide it so the side nearest the barrel is at the prescribed weight marking, aligning the arrow on the ring to the line between the weight and lbs, as shown in the pictogram.
(2) Lock the ring in place by making a 1/4 turn to the right. Ensure it is locked (it should no longer slide).
(3) Make sure that the horse's mouth contains no feed.
(4) Remove the cover from the tip of the syringe.
(5) Insert the syringe tip into the horse's mouth at the space between the teeth.
(6) Depress the plunger as far as it will go, depositing paste on the back of the tongue.
(7) Immediately raise the horse's head for a few seconds after dosing.

WARNINGS

WARNING: Do not use in horses intended for human consumption.

Not for use in humans. Keep this and all drugs out of reach of children. Refrain from smoking and eating when handling. Wash hands after use. Avoid contact with eyes. The Safety Data Sheet (SDS) contains more detailed occupational safety information. To report suspected adverse drug events, for technical assistance, or to obtain a copy of the SDS contact Strideguardpet. at 1-800-821-5570. For additional information about adverse drug experience reporting for animal drugs, contact FDA at 1-888-FDA-VETS or www.fda.gov/reportanimalae.

PRECAUTIONS

PRECAUTIONS: IVERMECTIN (ivermectin paste) has been formulated specifically for use in horses only. This product should not be used in other animal species as severe adverse reactions, including fatalities in dogs, may result.

OTHER WARNINGS: Parasite resistance may develop to any dewormer, and has been reported for most classes of dewormers.

Treatment with a dewormer used in conjunction with parasite management practices appropriate to the geographic area and the animal(s) to be treated may slow the development of parasite resistance.

Fecal examinations or other diagnostic tests and parasite management history should be used to determine if the product is appropriate for the herd prior to the use of any dewormer. Following the use of any dewormer, effectiveness of treatment should be monitored (for example, with the use of a fecal egg count reduction test or another appropriate method).

A decrease in a drug's effectiveness over time as calculated by fecal egg count reduction tests may indicate the development of resistance to the dewormer administered. Your parasite management plan should be adjusted accordingly based on regular monitoring.

Environmental Safety: Ivermectin and excreted ivermectin residues may adversely affect aquatic organisms. Do not contaminate ground or surface water. Dispose of the syringe in an approved landfill or by incineration.

INFORMATION FOR HORSE OWNERS: Swelling and itching reactions after treatment with IVERMECTIN (ivermectin paste) have occurred in horses carrying heavy infections of neck threadworm (Onchocerca sp.) microfilariae. These reactions were most likely the result of microfilariae dying in large numbers. Symptomatic treatment may be advisable. Consult your veterinarian should any such reactions occur. Healing of summer sores involving extensive tissue changes may require other appropriate therapy in conjunction with treatment with IVERMECTIN. Reinfection, and measures for its prevention, should also be considered. Consult your veterinarian if the condition does not improve.

Distributed by:

YASMEEN GLOBAL TRADERS LLC

30 N Gould St Ste 53477

sheridan, Wy 82801

PRINCIPAL DISPLAY PANEL - 0.21 oz (6.08g)

Keep out of reach of children

For Oral Use in Horses Only

IVERMECTIN
(ivermectin paste) 1.87%

Net Wt. 0.21 oz (6.08)
Contents will treat up to 1250 lb body weight

Approved by FDA under # 200-336

Apple Flavored